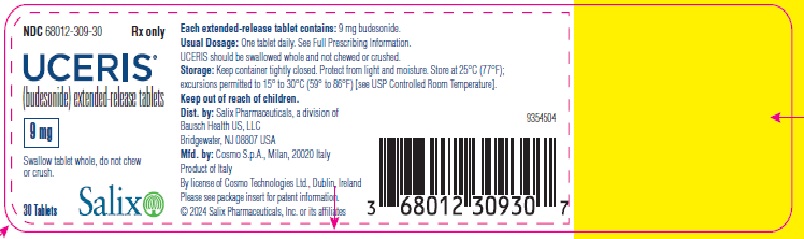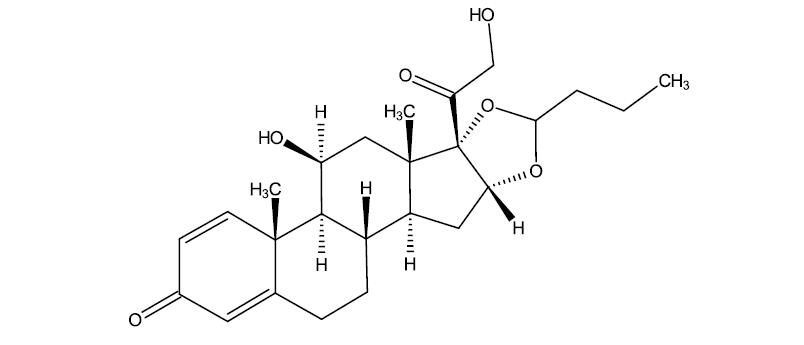 DRUG LABEL: Uceris
NDC: 68012-309 | Form: TABLET, EXTENDED RELEASE
Manufacturer: Santarus Inc.
Category: prescription | Type: HUMAN PRESCRIPTION DRUG LABEL
Date: 20241021

ACTIVE INGREDIENTS: BUDESONIDE 9 mg/1 1
INACTIVE INGREDIENTS: STEARIC ACID; SOYBEAN LECITHIN; LACTOSE, UNSPECIFIED FORM; SILICON DIOXIDE; MAGNESIUM STEARATE; METHACRYLIC ACID AND ETHYL ACRYLATE COPOLYMER; TALC; TRIETHYL CITRATE; TITANIUM DIOXIDE; MICROCRYSTALLINE CELLULOSE; HYDROXYPROPYL CELLULOSE, UNSPECIFIED

HIGHLIGHTS OF PRESCRIBING INFORMATION

These highlights do not include all the information needed to use UCERIS safely and effectively. See full prescribing information for UCERIS.
UCERIS® (budesonide) extended-release tablets, for oral use
Initial U.S. Approval: 1997

RECENT MAJOR CHANGES

Warnings and Precautions,

Immunosuppression and Increased Risk of Infection (5.3) 06/2024

Kaposi’s Sarcoma (5.4) 06/2024

1 INDICATIONS AND USAGE

UCERIS (budesonide) is a glucocorticosteroid indicated for the induction of remission in patients with active, mild to moderate ulcerative colitis. (1)

2 DOSAGE AND ADMINISTRATION

The recommended dosage for the induction of remission in adult patients with active, mild to moderate ulcerative colitis is one 9 mg tablet to be taken once daily in the morning with or without food for up to 8 weeks. (2.1)

3 DOSAGE FORMS AND STRENGTHS

Extended-release tablets: 9 mg (3)

4 CONTRAINDICATIONS

- Known hypersensitivity to budesonide or any of the ingredients in UCERIS tablets (4)

5 WARNINGS AND PRECAUTIONS

- Hypercorticism and adrenal suppression: May occur with treatment; monitor for signs and symptoms. (5.1)
- Transferring patients from systemic glucocorticoids:Risk of impaired adrenal function when transferring from glucocorticoid treatment with higher systemic effects to glucocorticoid treatment with lower systemic effects, such as UCERIS. Taper patients slowly from systemic corticosteroids if transferring to UCERIS. (5.2)
- Immunosuppression and Increased Risk of Infection:Increased risk of viral, bacterial, fungal, protozoal and helminthic infections, including potentially fatal varicella and measles infection. Monitor patients for new or worsening infection and consider drug discontinuation. Avoid use in patients with fungal infections, Strongyloidesinfestation, cerebral malaria and ocular herpes simplex. Screen for hepatitis B infection. (5.3)
- Kaposi’s Sarcoma:Reported to occur in patients receiving corticosteroid therapy, most often for chronic conditions. (5.4)

6 ADVERSE REACTIONS

Most common adverse reactions (incidence ≥2%) are headache, nausea, decreased blood cortisol, upper abdominal pain, fatigue, flatulence, abdominal distension, acne, urinary tract infection, arthralgia, and constipation. (6.1)

To report SUSPECTED ADVERSE REACTIONS, contact Salix Pharmaceuticals at 1-800-321-4576 or FDA at 1-800-FDA-1088 or www.fda.gov/medwatch.

7 DRUG INTERACTIONS

- Avoid cytochrome P450 3A4 inhibitors (e.g., ketoconazole, grapefruit juice). May cause increased systemic corticosteroid effects. (2.2, 7, 12.3)

8 USE IN SPECIFIC POPULATIONS

- Pregnancy:Based on animal data, may cause fetal harm. (8.1)
- Hepatic Impairment: Monitor patients for signs and/or symptoms of hypercorticism. (5.5, 8.6)

FULL PRESCRIBING INFORMATION

1 INDICATIONS AND USAGE

UCERIS®extended-release tablets are indicated for the induction of remission in patients with active, mild to moderate ulcerative colitis.

2 DOSAGE AND ADMINISTRATION

2.1 Mild to Moderate Ulcerative Colitis

The recommended dosage for the induction of remission in adult patients with active, mild to moderate ulcerative colitis is 9 mg taken orally once daily in the morning with or without food for up to 8 weeks. UCERIS should be swallowed whole and not chewed or crushed.

2.2 CYP3A4 Inhibitors

If concomitant administration with ketoconazole, or any other CYP3A4 inhibitor, is indicated, patients should be closely monitored for increased signs and/or symptoms of hypercorticism. Avoid grapefruit juice, which is known to inhibit CYP3A4, when taking UCERIS. In these cases, discontinuation of UCERIS or the CYP3A4 inhibitor should be considered [see Drug Interactions (7) and Clinical Pharmacology (12.3)].

3 DOSAGE FORMS AND STRENGTHS

White, round, biconvex extended-release tablets debossed with “MX9” .Each extended-release tablet contains 9 mg budesonide.

4 CONTRAINDICATIONS

UCERIS is contraindicated in patients with hypersensitivity to budesonide or any of the ingredients of UCERIS. Anaphylactic reactions have occurred with other budesonide formulations [see Adverse Reactions (6.2)].

5 WARNINGS AND PRECAUTIONS

5.1 Hypercorticism and Adrenal Axis Suppression

Systemic effects such as hypercorticism and adrenal suppression may occur with use corticosteroids, including UCERIS. Monitor patients for signs and symptoms of hypercorticism and adrenal axis suppression during treatment with UCERIS.

Patients with moderate to severe liver disease should be monitored for increased signs and/or symptoms of hypercorticism. Discontinuing the use of UCERIS tablets should be considered in these patients [see Use in Specific Populations (8.6)].

Glucocorticosteroids, including UCERIS, can reduce the response of the hypothalamus-pituitary-adrenal (HPA) axis to stress. In situations where patients are subject to surgery or other stress situations, supplementation with a systemic glucocorticosteroid is recommended.

5.2 Transferring Patients from Systemic Glucocorticosteroid Therapy

Care is needed in patients who are transferred from glucocorticosteroid treatment with higher systemic effects to glucocorticosteroids with lower systemic effects, such as UCERIS, since symptoms attributed to withdrawal of steroid therapy, including those of acute adrenal suppression or benign intracranial hypertension, may develop. Adrenocortical function monitoring may be required in these patients, and the dose of glucocorticosteroid treatment with high systemic effects should be reduced cautiously.

Replacement of systemic glucocorticosteroids with UCERIS tablets may unmask allergies (e.g., rhinitis and eczema), which were previously controlled by the systemic drug.

5.3 Immunosuppression and Increased Risk of Infection

Corticosteroids, including UCERIS, suppress the immune system and increase the risk of infection with any pathogen, including viral, bacterial, fungal, protozoan, or helminthic pathogens. Corticosteroids can:

- Reduce resistance to new infections
- Exacerbate existing infections
- Increase the risk of disseminated infections
- Increase the risk of reactivation or exacerbation of latent infections
- Mask some signs of infection

Corticosteroid-associated infections can be mild but can be severe and at times fatal. The rate of infectious complications increases with increasing corticosteroid dosages.

Monitor patients for the development of infection and consider discontinuation of UCERIS if the patient develops an infection while on treatment.

Tuberculosis

If UCERIS is used in patients with latent tuberculosis or tuberculin reactivity, reactivation of tuberculosis may occur. Closely monitor such patients for reactivation. During prolonged UCERIS therapy, patients with latent tuberculosis or tuberculin reactivity should receive chemoprophylaxis.

Varicella Zoster and Measles Viral Infections

Varicella and measles can have a serious or even fatal course in non-immune patients taking corticosteroids, including UCERIS. In corticosteroid-treated patients who have not had these diseases or are non-immune, particular care should be taken to avoid exposure to varicella and measles:

- If a UCERIS-treated patient is exposed to varicella, prophylaxis with varicella zoster immune globulin may be indicated. If varicella develops, treatment with antiviral agents may be considered.
- If a UCERIS-treated patient is exposed to measles, prophylaxis with immunoglobulin may be indicated.

Hepatitis B Virus Reactivation

Hepatitis B virus reactivation can occur in patients who are hepatitis B carriers treated with immunosuppressive dosages of corticosteroids, including UCERIS. Reactivation can also occur infrequently in corticosteroid-treated patients who appear to have resolved hepatitis B infection.

Screen patients for hepatitis B infection before initiating immunosuppressive (e.g., prolonged) treatment with UCERIS. For patients who show evidence of hepatitis B infection, recommend consultation with physicians with expertise in managing hepatitis B regarding monitoring and consideration for hepatitis B antiviral therapy.

Fungal Infections

Corticosteroids, including UCERIS, may exacerbate systemic fungal infections; therefore, avoid UCERIS use in the presence of such infections. For patients on chronic UCERIS therapy who develop systemic fungal infections, UCERIS withdrawal or dosage reduction is recommended.

Amebiasis

Corticosteroids, including UCERIS, may activate latent amebiasis. Therefore, it is recommended that latent amebiasis or active amebiasis be ruled out before initiating UCERIS in patients who have spent time in the tropics or patients with unexplained diarrhea.

Strongyloides Infestation

Avoid UCERIS in patients with known or suspected Strongyloides (threadworm) infection. Corticosteroids-induced immunosuppression may lead to Strongyloides superinfection and dissemination with widespread larval migration, often accompanied by severe enterocolitis and potentially fatal gram-negative septicemia.

Cerebral Malaria

Avoid corticosteroids, including UCERIS, in patients with cerebral malaria.

5.4 Kaposi’s Sarcoma

Kaposi’s sarcoma has been reported to occur in patients receiving corticosteroid therapy, most often for chronic conditions. Discontinuation of corticosteroids may result in clinical improvement of Kaposi’s sarcoma.

5.5 Increased Systemic Glucocorticoid Susceptibility

Reduced liver function affects the elimination of glucocorticosteroids, and increased systemic availability of oral budesonide has been demonstrated in patients with liver cirrhosis [see Use in Specific Populations (8.6)] .

5.6 Other Glucocorticosteroid Effects

Caution should be taken in patients with hypertension, diabetes mellitus, osteoporosis, peptic ulcer, glaucoma or cataracts, or with a family history of diabetes or glaucoma, or with any other condition where glucocorticosteroids may have unwanted effects.

6 ADVERSE REACTIONS

Systemic glucocorticosteroid use may result in the following:

- Hypercorticism and Adrenal Suppression [see Warnings and Precautions (5.1)]
- Symptoms of steroid withdrawal in those patients transferring from Systemic Glucocorticosteroid Therapy [see Warnings and Precautions (5.2)]
- Immunosuppression and Increased Risk of Infection [see Warnings and Precautions (5.3)]
- Kaposi’s Sarcoma [see Warnings and Precautions (5.4)]
- Increased Systemic Glucocorticoid Susceptibility [see Warnings and Precautions (5.5)]
- Other Glucocorticosteroid Effects [see Warnings and Precautions (5.6)]

6.1 Clinical Trials Experience

Because clinical trials are conducted under widely varying conditions, adverse reaction rates observed in the clinical trials of a drug cannot be directly compared to rates in the clinical trials of another drug and may not reflect the rates observed in practice.

The safety of UCERIS has been evaluated in controlled and open-label clinical trials which enrolled a combined total of 1,105 patients with ulcerative colitis.

In two 8-week, placebo-controlled studies in patients with active disease (Study 1 and Study 2), a total of 255 patients received UCERIS 9 mg, 254 patients received UCERIS 6 mg, and 258 patients received placebo. They ranged in age from 18-77 years (mean=43), 56% were male, and 75% were Caucasian. The most common adverse reactions were headache, nausea, decreased blood cortisol, upper abdominal pain, fatigue, flatulence, abdominal distension, acne, urinary tract infection, arthralgia, and constipation. The adverse reactions occurring in 2% or more of patients on therapy with UCERIS 9 mg are summarized in Table 1.

Table 1: Summary of Adverse Reactions in Two Placebo-Controlled Trials Experienced by at Least 2% of the UCERIS 9 mg Group (Studies 1 and 2)
 | UCERIS 9 mg (N=255) n (%) | UCERIS 6 mg (N=254) n (%) | Placebo (N=258) n (%)
Headache | 29 (11.4) | 37 (14.6) | 27 (10.5)
Nausea | 13 (5.1) | 12 (4.7) | 11 (4.3)
Decreased blood cortisol | 11 (4.3) | 6 (2.4) | 1 (0.4)
Upper abdominal pain | 10 (3.9) | 8 (3.1) | 5 (1.9)
Fatigue | 8 (3.1) | 5 (2.0) | 5 (1.9)
Flatulence | 6 (2.4) | 8 (3.1) | 5 (1.9)
Abdominal distension | 6 (2.4) | 4 (1.6) | 2 (0.8)
Acne | 6 (2.4) | 2 (0.8) | 5 (1.9)
Urinary tract infection | 5 (2.0) | 1 (0.4) | 1 (0.4)
Arthralgia | 5 (2.0) | 5 (2.0) | 4 (1.6)
Constipation | 5 (2.0) | 1 (0.4) | 2 (0.8)

Of UCERIS 9 mg patients, a total of 15% discontinued treatment due to any adverse event (including adverse reactions) compared with 17% in the placebo group.

Table 2 summarizes the percentages of patients reporting glucocorticoid-related effects in the 2 placebo-controlled studies.

Table 2: Summary of Glucocorticoid-Related Effects in Two Placebo-Controlled Trials (Studies 1 and 2)
 | UCERIS 9 mg (N=255) n (%) | UCERIS 6 mg (N=254) n (%) | Placebo (N=258) n (%)
Overall | 26 (10.2) | 19 (7.5) | 27 (10.5)
Mood changes | 9 (3.5) | 10 (3.9) | 11 (4.3)
Sleep changes | 7 (2.7) | 10 (3.9) | 12 (4.7)
Insomnia | 6 (2.4) | 6 (2.4) | 8 (3.1)
Acne | 6 (2.4) | 2 (0.8) | 5 (1.9)
Moon face | 3 (1.2) | 3 (1.2) | 4 (1.6)
Fluid retention | 2 (0.8) | 3 (1.2) | 3 (1.2)
Hirsutism | 1 (0.4) | 0 | 0
Striae rubrae | 0 | 0 | 2 (0.8)
Flushing | 0 | 1 (0.4) | 3 (1.2)

No clinically significant differences were observed with respect to the overall percentages of patients with any glucocorticoid-related effects between UCERIS and placebo after 8 weeks of induction therapy.

Study 3 was an open-label study evaluating UCERIS 9 mg once daily for 8 weeks in 60 patients who had previously completed an 8-week induction study (Study 1) but had not achieved remission. Among patients who took UCERIS 9 mg up to 16 weeks cumulatively across Study 1 and Study 3 combined, similar rates of adverse reactions and glucocorticoid-related effects were seen compared to those who took UCERIS 9 mg for 8 weeks in Study 1.

In Study 4, the safety of long-term treatment with UCERIS 6 mg was evaluated in a placebo-controlled 12-month maintenance study of 123 patients. Patients who had previously completed 8 weeks of therapy in any induction study (Study 1, 2, or 3) and were in remission were randomized to UCERIS 6 mg or placebo once daily for 12 months. In patients who took UCERIS 6 mg for up to 12 months, similar rates of adverse reactions were seen between placebo and UCERIS 6 mg. After up to 12 months of study treatment, 77% (27/35) of the patients in the UCERIS 6 mg and 74% (29/39) of the patients in the placebo treatment groups had normal bone density scans.

In Study 4, the glucocorticoid-related effects were similar in patients with up to 12 months of therapy with UCERIS 6 mg and placebo (Table 3).

Table 3: Summary of Glucocorticoid-Related Effects Over 12-Month Treatment (Study 4)
 | UCERIS 6 mg (N=62) n (%) | Placebo (N=61) n (%)
Overall | 9 (14.5) | 7 (11.5)
- Insomnia | 4 (6.5) | 4 (6.6)
- Mood changes | 4 (6.5) | 2 (3.3)
- Moon face | 3 (4.8) | 3 (4.9)
- Sleep changes | 3 (4.8) | 3 (4.9)
- Acne | 3 (4.8) | 0
- Hirsutism | 3 (4.8) | 0
- Flushing | 1 (1.6) | 1 (1.6)
- Fluid retention | 1 (1.6) | 1 (1.6)

6.2 Postmarketing Experience

In addition to adverse events reported from clinical trials, the following adverse reactions have been identified during post-approval use of oral budesonide. Because these reactions are reported voluntarily from a population of uncertain size, it is not always possible to reliably estimate their frequency or establish a causal relationship to drug exposure. These events have been chosen for inclusion due to either their seriousness, frequency of reporting or causal connection to UCERIS, or a combination of these factors.

Gastrointestinal Disorders: diarrhea, rectal bleeding

General Disorders and Administrative Site Conditions:peripheral edema

Immune System Disorders:anaphylactic reactions

Musculoskeletal and Connective Tissue Disorders:muscle cramps/spasms

Nervous System Disorders:benign intracranial hypertension, dizziness

Psychiatric Disorders:mood swings

Skin and Subcutaneous Tissue Disorders:rash

Vascular Disorders:increased blood pressure

7 DRUG INTERACTIONS

7.1 Interaction with CYP3A4 Inhibitors

Concomitant oral administration of ketoconazole (a known inhibitor of CYP3A4 activity in the liver and in the intestinal mucosa) caused an eight-fold increase of the systemic exposure to oral budesonide. If treatment with inhibitors of CYP3A4 activity (such as ketoconazole, itraconazole, ritonavir, indinavir, saquinavir, erythromycin) is indicated, discontinuation of UCERIS should be considered. After extensive intake of grapefruit juice (which inhibits CYP3A4 activity predominantly in the intestinal mucosa), the systemic exposure for oral budesonide increased about two times. Ingestion of grapefruit or grapefruit juice should be avoided in connection with UCERIS administration [see Dosage and Administration (2) and Clinical Pharmacology (12.3)].

7.2 Inhibitors of Gastric Acid Secretion

Since the dissolution of the coating of UCERIS is pH dependent, the release properties and uptake of the compound may be altered when UCERIS is used after treatment with gastric acid reducing agents (e.g., proton pump inhibitors (PPIs), H2blockers and antacids).

8 USE IN SPECIFIC POPULATIONS

8.1 Pregnancy

Risk Summary

Limited published studies report on the use of budesonide in pregnant women; however, the data are insufficient to inform a drug-associated risk for major birth defects and miscarriage. There are clinical considerations (see Clinical Considerations).In animal reproduction studies with pregnant rats and rabbits, subcutaneous administration of budesonide during organogenesis at doses 0.5 times and 0.05 times, respectively, the maximum recommended human dose, resulted in increased fetal loss, decreased pup weights, and skeletal abnormalities. Maternal toxicity was observed in both rats and rabbits at these dose levels (see Data). Based on animal data, advise pregnant women of the potential risk to a fetus. The estimated background risk of major birth defects and miscarriage of the indicated population is unknown. All pregnancies have a background risk of birth defect, loss, or other adverse outcomes. In the U.S. general population, the estimated background risk of major birth defects and miscarriage in clinically recognized pregnancies is 2% to 4%, and 15% to 20%, respectively.

Clinical Considerations

Disease-Associated Maternal and/or Embryofetal Risk

Published data suggest that increased disease activity is associated with the risk of developing adverse pregnancy outcomes in women with ulcerative colitis. Adverse pregnancy outcomes include preterm delivery (before 37 weeks of gestation), low birth weight (less than 2500 g) infants, and small for gestational age at birth.

Fetal/Neonatal Adverse Reactions

Hypoadrenalism may occur in infants born of mothers receiving corticosteroids during pregnancy. Infants should be carefully observed for signs of hypoadrenalism, such as poor feeding, irritability, weakness, and vomiting, and managed accordingly [see Warnings and Precautions (5.1)].

Data

Animal Data

Budesonide was teratogenic and embryolethal in rabbits and rats. In an embryofetal development study in pregnant rats dosed subcutaneously with budesonide during the period of organogenesis from gestation days 6-15 there were effects on fetal development and survival at subcutaneous doses up to approximately 500 mcg/kg in rats (approximately 0.5 times the maximum recommended human dose on a body surface area basis). In an embryofetal development study in pregnant rabbits dosed during the period of organogenesis from gestation days 6-18, there was an increase in maternal abortion, and effects on fetal development and reduction in litter weights at subcutaneous doses up to approximately 25 mcg/kg in rabbits (approximately 0.05 times the maximum recommended human dose on a body surface area basis). Maternal toxicity, including reduction in body weight gain, was observed at subcutaneous doses of 5 mcg/kg in rabbits (approximately 0.01 times the maximum recommended human dose on a body surface area basis) and 500 mcg/kg in rats

(approximately 0.5 times the maximum recommended human dose on a body surface area basis). In a peri- and postnatal development study, rats dosed subcutaneously with budesonide during the period of Day 15 post coitum to Day 21 postpartum, budesonide had no effects on delivery but did have an effect on growth and development of offspring. In addition, offspring survival was reduced, and surviving offspring had decreased mean body weights at birth and during lactation at exposures 0.02 times the MRHD (on a mg/m^2basis at maternal subcutaneous doses of 20 mcg/kg/day and higher). These findings occurred in the presence of maternal toxicity.

8.2 Lactation

Risk Summary

Lactation studies have not been conducted with UCERIS or other oral budesonide products and no information is available on the effects of budesonide on the breastfed infant or the effects of the drug on milk production. One published study reports that budesonide is present in human milk following maternal inhalation of budesonide (see Data). The developmental and health benefits of breastfeeding should be considered along with the mother’s clinical need for UCERIS and any potential adverse effects on the breastfed infant from UCERIS, or from the underlying maternal condition.

Data

One published study reports that budesonide is present in human milk following maternal inhalation of budesonide which resulted in infant doses approximately 0.3% to 1% of the maternal weight-adjusted dosage and a milk/plasma ratio ranging between 0.4 and 0.5. Budesonide plasma concentrations were not detected, and no adverse events were noted in the breastfed infants following maternal use of inhaled budesonide. The recommended daily dose of UCERIS is higher (9 mg daily) compared with inhaled budesonide (up to 800 mcg daily) given to mothers in the above described study. The maximum budesonide plasma concentration following a 9 mg daily dose (in both single- and repeated-dose pharmacokinetic studies) of oral budesonide is approximately 5 to 10 nmol/L which is up to 10 times higher than the 1 to 2 nmol/L for a 800 mcg daily dose of inhaled budesonide at steady state in the above inhalation study. Assuming the coefficient of extrapolation between the inhaled and oral doses is constant across all dose levels, at therapeutic doses of UCERIS, budesonide exposure to the nursing child may be up to 10 times higher than that by budesonide inhalation.

8.4 Pediatric Use

Safety and effectiveness of UCERIS in pediatric patients have not been established. Glucocorticosteroids, such as UCERIS, may cause a reduction of growth velocity in pediatric patients.

8.5 Geriatric Use

Clinical studies of UCERIS did not include sufficient numbers of subjects aged 65 and older to determine whether they respond differently from younger subjects. Other reported clinical experience has not identified differences in responses between the elderly and younger patients. In general, UCERIS should be used cautiously in elderly patients due to the potential for decreased hepatic, renal, or cardiac function, and of concomitant disease or other drug therapy.

8.6 Hepatic Impairment

Patients with moderate to severe liver disease should be monitored for increased signs and/or symptoms of hypercorticism. Discontinuing the use of UCERIS tablets should be considered in these patients [see Warnings and Precautions(5.5)].

10 OVERDOSAGE

Reports of acute toxicity and/or death following overdosage of glucocorticosteroids are rare. Treatment consists of immediate gastric lavage or emesis followed by supportive and symptomatic therapy.

If glucocorticosteroids are used at excessive doses for prolonged periods, systemic glucocorticosteroid effects, such as hypercorticism and adrenal suppression may occur. For chronic overdosage in the face of severe disease requiring continuous steroid therapy, the dosage may be reduced temporarily.

Single oral budesonide doses of 200 and 400 mg/kg were lethal in female and male mice, respectively. The signs of acute toxicity were decreased motor activity, piloerection and generalized edema.

11 DESCRIPTION

UCERIS®(budesonide) extended-release tablets, for oral administration, contain budesonide, a synthetic corticosteroid, as the active ingredient. Budesonide is designated chemically as (RS)-11β, 16α, 17,21 tetrahydroxypregna-1,4-diene-3,20-dione cyclic 16,17-acetal with butyraldehyde.

Budesonide is provided as a mixture of two epimers (22R and 22S). The empirical formula of budesonide is C25H34O6 and its molecular weight is 430.5. Its structural formula is:

Budesonide is a white to off-white, odorless, crystalline powder that is practically insoluble in water, sparingly soluble in alcohol, and freely soluble in chloroform.

UCERIS, a delayed and extended-release tablet, is coated with a polymer film, which breaks down at or above pH 7. The tablet core contains budesonide with polymers that provide for extended release of budesonide.

Each tablet contains the following inactive ingredients: stearic acid, lecithin, microcrystalline cellulose, hydroxypropyl cellulose, lactose, silicon dioxide, magnesium stearate, methacrylic acid copolymer types A and B, talc, triethyl citrate, and titanium dioxide.

12 CLINICAL PHARMACOLOGY

12.1 Mechanism of Action

Budesonide has a high topical glucocorticosteroid (GCS) activity and substantial first-pass elimination. The formulation contains budesonide in an extended-release tablet core. The tablet core is enteric coated to protect dissolution in gastric juice which delays budesonide release until exposure to a pH ≥7 in the small intestine. Upon disintegration of the coating, the core matrix provides extended release of budesonide in a time dependent manner.

12.2 Pharmacodynamics

Budesonide has a high glucocorticoid effect and a weak mineralocorticoid effect, and the affinity of budesonide to GCS receptors, which reflects the intrinsic potency of the drug, is about 200-fold that of cortisol and 15-fold that of prednisolone.

Treatment with systemically active GCS, including UCERIS, is associated with a suppression of endogenous cortisol concentrations and an impairment of the hypothalamus-pituitary-adrenal (HPA) axis function. Markers, indirect and direct, of this are cortisol levels in plasma or urine and response to ACTH stimulation.

In a study assessing the response to ACTH stimulation test in patients treated with UCERIS 9 mg once daily, the proportion of patients with abnormal response was 47% at 4 weeks and 79% at 8 weeks.

12.3 Pharmacokinetics

Absorption

Following single oral administration of UCERIS 9 mg in healthy subjects, peak plasma concentration (Cmax) was 1.35 ± 0.96 ng/mL, the time to peak concentration (Tmax) on average was 13.3 ± 5.9 hours, although it varied across different individual patients, and the area under the plasma concentration time curve (AUC) was approximately 16.43 ± 10.52 ng·hr/mL. The pharmacokinetic parameters of UCERIS 9 mg have a high degree of variability among subjects. There was no accumulation of budesonide with respect to both AUC and Cmaxfollowing 7 days of UCERIS 9 mg once daily dosing.

Food Effect

A food-effect study involving administration of UCERIS to healthy volunteers under fasting conditions and with a high-fat meal indicated that the Cmaxwas decreased by 27% while there was no significant decrease in AUC. Additionally, a mean delay in absorption lag time of 2.4 hours was observed under fed conditions.

Distribution

The mean volume of distribution (VSS) of budesonide varies between 2.2 and 3.9 L/kg in healthy subjects and in patients. Plasma protein binding is estimated to be 85 to 90% in the concentration range 1 to 230 nmol/L, independent of gender. The erythrocyte/plasma partition ratio at clinically relevant concentrations is about 0.8.

Elimination

Metabolism

Following absorption, budesonide is subject to high first-pass metabolism (80-90%). In vitroexperiments in human liver microsomes demonstrate that budesonide is rapidly and extensively biotransformed, mainly by CYP3A4, to its 2 major metabolites, 6β-hydroxy budesonide and 16α-hydroxy prednisolone. The glucocorticoid activity of these metabolites is negligible (<1/100) in relation to that of the parent compound. In vivoinvestigations with intravenous doses in healthy subjects are in agreement with the in vitrofindings and demonstrate that budesonide has a high plasma clearance, 0.9-1.8 L/min. These high plasma clearance values approach the estimated liver blood flow, and, accordingly, suggest that budesonide is a high hepatic clearance drug. The plasma elimination half-life, t1/2, after administration of intravenous doses ranges between 2 and 3.6 hours.

Excretion

Budesonide is excreted in urine and feces in the form of metabolites. After oral as well as intravenous administration of micronized [^3H]-budesonide, approximately 60% of the recovered radioactivity is found in urine. The major metabolites, including 6β-hydroxy budesonide and 16α-hydroxy prednisolone, are mainly renally excreted, intact or in conjugated forms. No unchanged budesonide is detected in urine.

Specific Populations

Patients with Renal Impairment

The pharmacokinetics of budesonide in patients with renal impairment have not been studied. Intact budesonide is not renally excreted, but metabolites are to a large extent, and might therefore reach higher levels in patients with impaired renal function. However, these metabolites have negligible corticosteroid activity as compared with budesonide (<1/100). Patients with Hepatic Impairment

In patients with liver cirrhosis, systemic availability of orally administered budesonide correlates with disease severity and is, on average, 2.5-fold higher compared with healthy controls. Patients with mild liver disease are minimally affected. Patients with severe liver dysfunction were not studied. Absorption parameters were not altered, and for the intravenous dose, no significant differences in CL or VSSwere observed.

Drug Interaction Studies

Budesonide is metabolized via CYP3A4. Potent inhibitors of CYP3A4 can increase the plasma levels of budesonide several-fold. Co-administration of ketoconazole results in an eight-fold increase in AUC of budesonide, compared to budesonide alone. Grapefruit juice, an inhibitor of gut mucosal CYP3A, approximately doubles the systemic exposure of oral budesonide. Conversely, induction of CYP3A4 can result in the lowering of budesonide plasma levels [see Dosage and Administration (2) and Drug Interactions (7)].Oral contraceptives containing ethinyl estradiol, which are also metabolized by CYP3A4, do not affect the pharmacokinetics of budesonide. Budesonide does not affect the plasma levels of oral contraceptives (i.e., ethinyl estradiol).

13 NONCLINICAL TOXICOLOGY

13.1 Carcinogenesis, Mutagenesis, Impairment of Fertility

Carcinogenicity

Carcinogenicity studies with budesonide were conducted in rats and mice. In a two-year study in Sprague-Dawley rats, budesonide caused a statistically significant increase in the incidence of gliomas in male rats at an oral dose of 50 mcg/kg (approximately 0.05 times the maximum recommended human dose on a body surface area basis). In addition, there were increased incidences of primary hepatocellular tumors in male rats at 25 mcg/kg (approximately 0.023 times the maximum recommended human dose on a body surface area basis) and above. No tumorigenicity was seen in female rats at oral doses up to 50 mcg/kg (approximately 0.05 times the maximum recommended human dose on a body surface area basis). In an additional two-year study in male Sprague-Dawley rats, budesonide caused no gliomas at an oral dose of 50 mcg/kg (approximately 0.05 times the maximum recommended human dose on a body surface area basis). However, it caused a statistically significant increase in the incidence of hepatocellular tumors at an oral dose of 50 mcg/kg (approximately 0.05 times the maximum recommended human dose on a body surface area basis). The concurrent reference glucocorticosteroids (prednisolone and triamcinolone acetonide) showed similar findings. In a 91-week study in mice, budesonide caused no treatment-related carcinogenicity at oral doses up to 200 mcg/kg (approximately 0.1 times the maximum recommended human dose on a body surface area basis).

Mutagenesis

Budesonide was not genotoxic in the Ames test, the mouse lymphoma cell forward gene mutation (TK+/-) test, the human lymphocyte chromosome aberration test, the Drosophila melanogastersex-linked recessive lethality test, the rat hepatocycte unscheduled DNA synthesis (UDS) test and the mouse micronucleus test.

Impairment of Fertility

In rats, budesonide had no effect on fertility at subcutaneous doses up to 80 mcg/kg (approximately 0.07 times the maximum recommended human dose on a body surface area basis). However, it caused a decrease in prenatal viability and viability in pups at birth and during lactation, along with a decrease in maternal body weight gain, at subcutaneous doses of 20 mcg/kg (approximately 0.02 times the maximum recommended human dose on a body surface area basis) and above. No such effects were noted at 5 mcg/kg (approximately 0.005 times the maximum recommended human dose on a body surface area basis).

14 CLINICAL STUDIES

Induction of Remission in Active, Mild to Moderate Ulcerative Colitis

Two similarly designed, randomized, double-blind, placebo-controlled studies were conducted in a total of 970 adult patients with active, mild to moderate ulcerative colitis (UC) which was defined as an Ulcerative Colitis Disease Activity Index (UCDAI of ≥4 and ≤10). Eight hundred ninety-nine of these patients had histology consistent with active UC; this was considered the primary analysis population. UCDAI is a four-component scale (total score of 0 to 12) that encompasses the clinical assessments of stool frequency, rectal bleeding, mucosal appearance and physician’s rating of disease activity (score of 0 to 3 for each of the components).

The baseline median UCDAI score in both studies was 7.

In Study 1, 56% of patients were male, and the median age was 42 years. In Study 2, 57% of patients were male, and the median age was 44 years. In Study 1, 50% of patients were Caucasian, 7% were African American, and 34% were Asian. In Study 2, more than 99% were Caucasian.

Both studies compared UCERIS 9 mg and 6 mg with placebo and included an active reference arm (a mesalamine 2.4 g in Study 1 and a budesonide* 9 mg not approved for the treatment of UC in Study 2). The primary endpoint was induction of remission after 8 weeks of treatment. Remission was defined as a UCDAI score of ≤1, with subscores of 0 for rectal bleeding, stool frequency, and mucosal appearance and with a ≥1 point reduction in an endoscopy-only score. In both studies, UCERIS 9 mg extended-release tablets demonstrated superiority to placebo in inducing remission (Table 4).

Table 4: Induction of Remission in Studies 1 and 2 Treatment Group
Treatment Group | Study 1 n/N (%) | Study 2 n/N (%)
UCERIS 9 mg | 22/123 (17.9) | 19/109 (17.4)
UCERIS 6 mg | 16/121 (13.2) | 9/109 (8.3)
Reference arm* | 15/124 (12.1) | 13/103 (12.6)
Placebo | 9/121 (7.4) | 4/89 (4.5)
Treatment difference between UCERIS 9 mg and placebo (95% CI)† | 10.4% (2.2%, 18.7%) | 12.9% (4.6%, 21.3%)

The primary analysis population included only patients that had histology consistent with active UC.

CI=Confidence Interval

*The reference arm in Study 1 is a delayed release mesalamine 2.4 g; the reference arm in Study 2 is a budesonide 9 mg not approved for the treatment of UC.

†p<0.025 for UCERIS 9 mg vs. placebo in both Studies 1 and 2 based on the Chi-square test (alpha=0.025)

15 REFERENCES

1. Rachmilewitz D. Coated mesalazine (5-aminosalicylic acid) versus sulphasalazine in the treatment of active ulcerative colitis: a randomised trial. BMJ. 1989;298:82-86.

16 HOW SUPPLIED/STORAGE AND HANDLING

UCERIS®(budesonide) extended-release tablets 9 mg are white, round, biconvex tablets and debossed with “MX9”. They

are supplied as follows:

NDC 68012-309-30 Bottles of 30 tablets

Store at 25°C (77°F); excursions permitted to 15°C to 30°C (59°F to 86°F). [See USP Controlled Room Temperature].

Keep container tightly closed. Protect from light and moisture.

17 PATIENT COUNSELING INFORMATION

Advise the patient to read the FDA-approved patient labeling (Patient Information).

Patients treated with UCERIS extended-release tablets should receive the following information and instructions. This information is intended to aid the patient in the safe and effective use of UCERIS.

Hypercorticism and Adrenal Suppression

Advise patients that UCERIS extended-release tablets may cause systemic glucocorticosteroid effects of hypercorticism and adrenal suppression. Taper slowly from systemic corticosteroids if transferring to UCERIS extended-release tablets [see Warnings and Precautions (5.1) and (5.2)] .

Immunosuppression and Increased Risk of Infection

Advise patients to avoid exposure to people with varicella (chicken pox) or measles. Advise patients to inform their healthcare provider if they are exposed to varicella or measles or develop a new or worsening infection [see Warnings and Precautions (5.3)].

Kaposi’s Sarcoma

Advise patients that Kaposi’s sarcoma has been reported in patients receiving corticosteroids for chronic conditions and to inform their healthcare provider if they experience signs or symptoms of Kaposi’s sarcoma [see Warnings and Precautions (5.4)].

How to Take UCERIS Extended-Release Tablets

Advise patients to swallow UCERIS extended-release tablets whole with water. Do not chew or crush. Avoid the consumption of grapefruit juice for the duration of UCERIS therapy [see Dosage and Administration (2)].

Pregnancy

Advise female patients that UCERIS may cause fetal harm and to inform their healthcare provider with a known or

suspected pregnancy [see Use in Specific Populations (8.1)] .

Distributed by:

Salix Pharmaceuticals, a division of

Bausch Health US, LLC

Bridgewater, NJ 08807 USA

Manufactured by:

Cosmo S.p.A.

Milan, 20045 Italy

By license of Cosmo Technologies Ltd., Dublin, Ireland

Patented. See https://patents.salix.com for US patent information.

UCERIS is a trademark of Salix Pharmaceuticals, Inc. or its affiliates.

© 2024 Salix Pharmaceuticals, Inc. or its affiliates

9464204

Patient Information

UCERIS®(u SAIR us)

(budesonide)

Extended-Release tablets

What are UCERIS extended-release tablets?

- UCERIS extended-release tablets are a prescription corticosteroid medicine used to help get active mild to moderate ulcerative colitis (UC) under control (induce remission).
- It is not known if UCERIS extended-release tablets are safe and effective in children.

Who should not take UCERIS extended-release tablets?

Do not take UCERIS extended-release tablets if:

- you are allergic to budesonide or any of the ingredients in UCERIS extended-release tablets. See the end of this leaflet for a complete list of ingredients in UCERIS extended-release tablets.

What should I tell my healthcare provider before taking UCERIS extended-release tablets?

Before you take UCERIS extended-release tablets tell your healthcare provider about all of your medical conditions, including if you:

- have liver problems.
- are planning to have surgery.
- have chickenpox or measles or have recently been near anyone with chickenpox or measles.
- have an infection, including fungal and threadworm (Strongyloides) infections.
- have or had a family history of diabetes, cataracts or glaucoma.
- have or had tuberculosis.
- have high blood pressure (hypertension).
- have decreased bone mineral density (osteoporosis).
- have stomach ulcers.
- have malaria of the brain (cerebral malaria).
- are pregnant or plan to become pregnant. UCERIS extended-release tablets may harm your unborn baby. Tell your healthcare provider if you are pregnant or think you are pregnant.
- are breastfeeding or plan to breastfeed. UCERIS extended-release tablets can pass into your breast milk and may harm your baby. You and your healthcare provider should decide if you will take UCERIS extended-release tablets or breastfeed. You should not do both.

Tell your healthcare provider about all the medicines you take,including prescription and over-the-counter medicines, vitamins, and herbal supplements. UCERIS extended-release tablets and other medicines may affect each other causing side effects.

Especially tell your healthcare provider if you take another medicine that contains corticosteroids for other conditions, such as allergies or asthma. Know the medicines you take. Keep a list of them to show your healthcare provider and pharmacist when you get a new medicine.

How should I take UCERIS extended-release tablets?

- Take UCERIS extended-release tablets exactly as your healthcare provider tells you to take them.
- Take UCERIS extended-release tablets 1 time each day in the morning with or without food.
- Take UCERIS extended-release tablets whole with water. Do not chew, crush, or break UCERIS extended-release tablets before swallowing.
- If you take too much of UCERIS extended-release tablets, call your healthcare provider right away or go to the nearest hospital emergency room.

What should I avoid while taking UCERIS extended-release tablets?

- Do not eat grapefruit or drink grapefruit juice while taking UCERIS extended-release tablets. Eating grapefruit or drinking grapefruit juice can increase the level of UCERIS extended-release tablets in your blood.

What are the possible side effects of UCERIS extended-release tablets?

UCERIS extended-release tablets may cause serious side effects, including:

- Effects of having too much corticosteroid medicine in your blood (hypercorticism).Long-time use of UCERIS extended-release tablets can cause you to have too much glucocorticosteroid medicine in your blood. Tell your healthcare provider if you have any of the following signs and symptoms of hypercorticism:
- acne
- bruise easily
- rounding of your face (moon face)
- ankle swelling
- thicker or more hair on your body and face
- a fatty pad or hump between your shoulders (buffalo hump)
- pink or purple stretch marks on the skin of your abdomen, thighs, breasts and arms
- Adrenal suppression.When UCERIS extended-release tablets are taken for a long period of time (chronic use), the adrenal glands do not make enough steroid hormones (adrenal suppression).
- Tell your healthcare provider if you are under stress or have any symptoms of adrenal suppression during treatment with UCERIS extended-release tablets including:
- tiredness
- weakness
- nausea
- vomiting
- low blood pressure
- Decreased ability of your body to fight infections (immunosuppression) and increased risk of infection.
- Corticosteroid medicines, including UCERIS, lower the ability of your immune system to fight infections and increase the risk of infections caused by viruses, bacteria, fungi, protozoan, or certain parasites. Corticosteroid medicines, including UCERIS, can also:
- make current infections worse
- increase the risk of infections spreading (disseminated)
- increase the risk of making infections active again or making infections worse that have not been active (latent)
- hide (mask) some signs of infection
- These infections can be mild but can be severe and lead to death. Your healthcare provider should check you closely for signs and symptoms of an infection while taking UCERIS. Tell your healthcare provider right away about any signs or symptoms of a new or worsening infection while taking UCERIS, including flu-like symptoms such as:
- fever
- chills
- stomach area (abdominal) pain
- aches
- diarrhea
- cough
- pain
- feeling tired
- nausea and vomiting
- Tuberculosis: If you have inactive (latent) tuberculosis, your tuberculosis may become active again while taking UCERIS. Your healthcare provider should check you closely for signs and symptoms of tuberculosis while taking UCERIS.
- Chickenpox and measles: People taking corticosteroid medicines, including UCERIS, who have not had chickenpox or measles, should avoid contact with people who have these diseases. Tell your healthcare provider right away if you come in contact with anyone who has chickenpox or measles.
- Hepatitis B virus (HBV) reactivation: If you are a carrier of HBV, the virus can become an active infection again while taking UCERIS. Your healthcare provider will test you for HBV before you start taking UCERIS.
- Amebiasis: Inactive (latent) amebiasis may become an active infection while taking UCERIS. Your healthcare provider should check you for amebiasis before you start taking UCERIS in people who have spent time in the tropics or have unexplained diarrhea.
- Kaposi’s sarcoma.Kaposi’s sarcoma has happened in people who received corticosteroid therapy, most often for treatment of long-lasting (chronic) conditions.
- Worsening of allergies.If you take certain other corticosteroid medicines to treat allergies, switching to UCERIS extended-release tablets may cause your allergies to come back. These allergies may include eczema (a skin disease) or rhinitis (inflammation inside your nose). Tell your healthcare provider if any of your allergies become worse while taking UCERIS extended-release tablets.

The most common side effects of UCERIS extended-release tablets include:

- headache
- nausea
- decreased blood
- cortisol levels
- stomach-area pain
- tiredness
- stomach or intestinal gas
- bloating
- acne
- urinary tract infection
- joint pain
- constipation

Tell your healthcare provider if you have any side effect that bothers you or that does not go away.

These are not all the possible side effects of UCERIS extended-release tablets. For more information, ask your healthcare provider or pharmacist.

Call your doctor for medical advice about side effects. You may report side effects to FDA at 1-800-FDA-1088.

How should I store UCERIS extended-release tablets?

- Store UCERIS extended-release tablets at room temperature, 77°F (25°C); excursions permitted to 59°F to 86°F (15°C to 30°C).
- Keep the bottle tightly closed to protect UCERIS extended-release tablets from light and moisture.

Keep UCERIS extended-release tablets and all medicines out of the reach of children.

General information about the safe and effective use of UCERIS extended-release tablets.

Medicines are sometimes prescribed for purposes other than those listed in a Patient Information leaflet. Do not use UCERIS extended-release tablets for a condition for which it was not prescribed. Do not give UCERIS extended-release tablets to other people, even if they have the same symptoms you have. It may harm them.

You can ask your healthcare provider or pharmacist for information about UCERIS extended-release tablets that is written for health professionals.

For more information, go to www.UCERIS.com or call 1-800-321-4576.

What are the ingredients in UCERIS extended-release tablets?

Active ingredient:budesonide

Inactive ingredients:stearic acid, lecithin, microcrystalline cellulose, hydroxypropyl cellulose, lactose, silicon dioxide, magnesium stearate, methacrylic acid copolymer types A and B, talc, triethyl citrate, and titanium dioxide.

Distributed by:

Salix Pharmaceuticals, a division of

Bausch Health US, LLC

Bridgewater, NJ 08807 USA

Manufactured by:

Cosmo S.p.A.

Milan, 20045 Italy

By license of Cosmo Technologies Ltd., Dublin, Ireland

Patented. See https://patents.salix.com for US patent information

UCERIS is a trademark of Salix Pharmaceuticals, Inc. or its affiliates.

© 2024 Salix Pharmaceuticals, Inc. or its affiliates

This Patient Information has been approved by the U.S. Food and Drug Administration. Revised: 06/2024

PRINCIPAL DISPLAY PANEL

PACKAGE LABEL – PRINCIPAL DISPLAY PANEL 9 mg

NDC68012-309-30

Rx only

UCERIS®

(budesonide) extended-release tablets

9 mg

Swallow tablet whole, do not chew or break.

30 Tablets

Salix